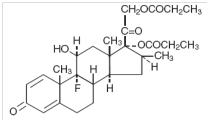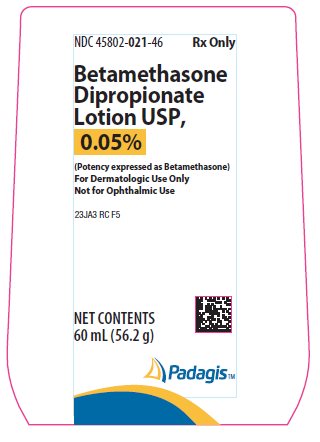 DRUG LABEL: Betamethasone Dipropionate
NDC: 45802-021 | Form: LOTION
Manufacturer: Padagis Israel Pharmaceuticals Ltd
Category: prescription | Type: HUMAN PRESCRIPTION DRUG LABEL
Date: 20220228

ACTIVE INGREDIENTS: BETAMETHASONE DIPROPIONATE 0.5 mg/1 g
INACTIVE INGREDIENTS: ISOPROPYL ALCOHOL; WATER; CARBOMER HOMOPOLYMER TYPE B (ALLYL PENTAERYTHRITOL CROSSLINKED); SODIUM HYDROXIDE

Rx Only
Betamethasone Dipropionate Lotion USP, 0.05%

(Potency expressed as Betamethasone)

For Dermatologic Use Only.

Not for Ophthalmic Use.

DESCRIPTION

Betamethasone Dipropionate Lotion USP, 0.05% contains betamethasone dipropionate, USP, a synthetic adrenocorticosteroid, for dermatologic use. Betamethasone, an analog of prednisolone, has high corticosteroid activity and slight mineralocorticoid activity. Betamethasone dipropionate is the 17, 21-dipropionate ester of betamethasone.

Chemically, betamethasone dipropionate is 9-fluoro-11β,17,21-trihydroxy-16β-methylpregna-1,4-diene-3,20-dione 17,21-dipropionate, with the empirical formula C28H37FO7, a molecular weight of 504.6, and the following structural formula:

Betamethasone dipropionate is a white to creamy white, odorless crystalline powder, insoluble in water.

Each gram of Betamethasone Dipropionate Lotion USP, 0.05% contains 0.64 mg betamethasone dipropionate (equivalent to 0.5 mg betamethasone) in a lotion base of carbomer homopolymer type B, isopropyl alcohol, and purified water. Sodium hydroxide is used to adjust pH.

CLINICAL PHARMACOLOGY

The corticosteroids are a class of compounds comprising steroid hormones, secreted by the adrenal cortex and their synthetic analogs. In pharmacologic doses corticosteroids are used primarily for their anti-inflammatory and/or immunosuppressive effects.

Topical corticosteroids, such as betamethasone dipropionate, are effective in the treatment of corticosteroid-responsive dermatoses primarily because of their anti-inflammatory, antipruritic, and vasoconstrictive actions. However, while the physiologic, pharmacologic, and clinical effects of the corticosteroids are well known, the exact mechanisms of their actions in each disease are uncertain. Betamethasone dipropionate, a corticosteroid, has been shown to have topical (dermatologic) and systemic pharmacologic and metabolic effects characteristic of this class of drugs.

Pharmacokinetics -

The extent of percutaneous absorption of topical corticosteroids is determined by many factors including the vehicle, the integrity of the epidermal barrier, and the use of occlusive dressings (see DOSAGE AND ADMINISTRATION).

Topical corticosteroids can be absorbed from normal intact skin. Inflammation and/or other disease processes in the skin increase percutaneous absorption. Occlusive dressings substantially increase the percutaneous absorption of topical corticosteroids (see DOSAGE AND ADMINISTRATION).

Once absorbed through the skin, topical corticosteroids are handled through pharmacokinetic pathways similar to systemically administered corticosteroids. Corticosteroids are bound to plasma proteins in varying degrees. Corticosteroids are metabolized primarily in the liver and are then excreted by the kidneys. Some of the topical corticosteroids and their metabolites are also excreted into the bile.

Twenty-five pediatric patients ages 6 to 12 years, with atopic dermatitis, were enrolled in an open-label, hypothalamic-pituitary-adrenal (HPA) axis safety study. Betamethasone dipropionate lotion 0.05% was applied twice daily for 2 to 3 weeks over a mean body surface area of 45% (range 35% to 72%). In 11 of 15 (73%) evaluable patients, adrenal suppression was indicated by either a < 5 mcg/dL pre-stimulation cortisol, or a cosyntropin post-stimulation cortisol < 18 mcg/dL and an increase of < 7 mcg/dL from the baseline cortisol. Studies performed with betamethasone dipropionate lotion 0.05% indicate that it is in the medium range of potency as compared with other topical corticosteroids.

INDICATIONS AND USAGE

Betamethasone Dipropionate Lotion USP, 0.05% is a medium-potency corticosteroid indicated for relief of the inflammatory and pruritic manifestations of corticosteroid-responsive dermatoses in patients 13 years and older.

CONTRAINDICATIONS

Betamethasone Dipropionate Lotion USP, 0.05% is contraindicated in patients who are hypersensitive to betamethasone dipropionate, to other corticosteroids, or to any ingredient in these preparations.

PRECAUTIONS

General -

Systemic absorption of topical corticosteroids has produced reversible hypothalamic-pituitary-adrenal (HPA) axis suppression, manifestations of Cushing's syndrome, hyperglycemia, and glucosuria in some patients.

Conditions which augment systemic absorption include the application of the more potent steroids, use over large surface areas, prolonged use, and the addition of occlusive dressings. Use of more than one corticosteroid-containing product at the same time may increase total systemic glucocorticoid exposure (see DOSAGE AND ADMINISTRATION).

Therefore, patients receiving a large dose of a potent topical steroid applied to a large surface area should be evaluated periodically for evidence of HPA axis suppression by using the urinary-free cortisol and ACTH stimulation tests. If HPA axis suppression is noted, an attempt should be made to withdraw the drug, to reduce the frequency of application, or to substitute a less potent steroid.

Recovery of HPA axis function is generally prompt and complete upon discontinuation of the drug. In an open-label pediatric study of 15 evaluable patients, of the 11 subjects who showed evidence of suppression, 6 subjects were tested 2 weeks after discontinuation of betamethasone dipropionate lotion 0.05%, and 4 of the 6 (67%) had complete recovery of HPA axis function. Infrequently, signs and symptoms of steroid withdrawal may occur, requiring supplemental systemic corticosteroids.

Pediatric patients may absorb proportionally larger amounts of topical corticosteroids and thus be more susceptible to systemic toxicity (see PRECAUTIONS - Pediatric Use).

If irritation develops, topical corticosteroids should be discontinued and appropriate therapy instituted.

In the presence of dermatological infections, the use of an appropriate antifungal or antibacterial agent should be instituted. If a favorable response does not occur promptly, the corticosteroid should be discontinued until the infection has been adequately controlled.

Information for Patients -

This information is intended to aid in the safe and effective use of this medication. It is not a disclosure of all possible adverse or intended effects.

Patients using topical corticosteroids should receive the following information and instructions:

1. This medication is to be used as directed by the physician. It is for external use only. Avoid contact with the eyes.

2. Patients should be advised not to use this medication for any disorder other than that for which it was prescribed.

3. The treated skin area should not be bandaged or otherwise covered or wrapped as to be occlusive (see DOSAGE AND ADMINISTRATION).

4. Patients should report any signs of local adverse reactions.

5. Other corticosteroid-containing products should not be used with Betamethasone Dipropionate Lotion USP, 0.05% without first talking to your physician.

Laboratory Tests -

The following tests may be helpful in evaluating HPA axis suppression:

Urinary-free cortisol test
ACTH stimulation test

Carcinogenesis, Mutagenesis, Impairment of Fertility -

Long-term animal studies have not been performed to evaluate the carcinogenic potential of betamethasone dipropionate.

Betamethasone was negative in the bacterial mutagenicity assay (Salmonella typhimurium and Escherichia coli), and in the mammalian cell mutagenicity assay (CHO/HGPRT). It was positive in the in-vitro human lymphocyte chromosome aberration assay, and equivocal in the in-vivo mouse bone marrow micronucleus assay. This pattern of response is similar to that of dexamethasone and hydrocortisone.

Reproductive studies with betamethasone dipropionate carried out in rabbits at doses of 1.0 mg/kg by the intramuscular route and in mice up to 33 mg/kg by the intramuscular route indicated no impairment of fertility except for dose-related increases in fetal resorption rates in both species. These doses are approximately 0.5 and 4 fold the estimated maximum human dose based on a mg/m^2 comparison, respectively.

Pregnancy: Teratogenic Effects: Pregnancy Category C-

Corticosteroids are generally teratogenic in laboratory animals when administered systemically at relatively low dosage levels.

Betamethasone dipropionate has been shown to be teratogenic in rabbits when given by the intramuscular route at doses of 0.05 mg/kg. This dose is approximately 0.03 fold the estimated maximum human dose based on a mg/m^2 comparison. The abnormalities observed included umbilical hernias, cephalocele and cleft palates.

Some corticosteroids have been shown to be teratogenic after dermal application in laboratory animals. There are no adequate and well-controlled studies in pregnant women on teratogenic effects from topically applied corticosteroids. Therefore, topical corticosteroids should be used during pregnancy only if the potential benefit justifies the potential risk to the fetus. Drugs of this class should not be used extensively on pregnant patients, in large amounts, or for prolonged periods of time.

Nursing Mothers -

It is not known whether topical administration of corticosteroids could result in sufficient systemic absorption to produce detectable quantities in breast milk. Systemically administered corticosteroids are secreted into breast milk in quantities not likely to have a deleterious effect on the infant. Nevertheless, caution should be exercised when topical corticosteroids are prescribed for a nursing woman.

Pediatric Use -

Use of Betamethasone Dipropionate Lotion USP, 0.05% in pediatric patients 12 years of age and younger is not recommended (see CLINICAL PHARMACOLOGY and ADVERSE REACTIONS sections). In an open-label study, 11 of 15 (73%) evaluable pediatric patients (aged 6 years-12 years old) using betamethasone dipropionate lotion 0.05% for treatment of atopic dermatitis for 2-3 weeks demonstrated adrenal suppression (see CLINICAL PHARMACOLOGY - Pharmacokinetics).

Pediatric patients may demonstrate greater susceptibility to topical corticosteroid-induced HPA axis suppression and Cushing’s syndrome than mature patients because of a larger skin surface area to body weight ratio.

Hypothalamic-pituitary-adrenal (HPA) axis suppression, Cushing's syndrome, and intracranial hypertension have been reported in pediatric patients receiving topical corticosteroids. Manifestations of adrenal suppression in pediatric patients include linear growth retardation, delayed weight gain, low plasma cortisol levels, and absence of response to ACTH stimulation. Manifestations of intracranial hypertension include bulging fontanelles, headaches, and bilateral papilledema.

Administration of topical corticosteroids to pediatric patients should be limited to the least amount compatible with an effective therapeutic regimen. Chronic corticosteroid therapy may interfere with the growth and development of pediatric patients.

ADVERSE REACTIONS

The following local adverse reactions are reported infrequently when betamethasone dipropionate lotion 0.05% is used as recommended in the DOSAGE AND ADMINISTRATION section. These reactions are listed in an approximate decreasing order of occurrence: burning, itching, irritation, dryness, folliculitis, hypertrichosis, acneiform eruptions, hypopigmentation, perioral dermatitis, allergic contact dermatitis, maceration of the skin, secondary infection, skin atrophy, striae, miliaria.

Adverse reactions reported to be possibly or probably related to treatment with betamethasone dipropionate lotion 0.05% during a pediatric study include: paresthesia (burning), erythema, erythematous rash, and dry skin. These adverse reactions each occurred in a different patient; 4% of the 25 patient population, respectively. An adverse reaction reported to be possibly or probably related to treatment in 2 different patients, 8%, of the 25 patients is puritis.

Systemic absorption of topical corticosteroids has produced reversible hypothalamic-pituitary-adrenal (HPA) axis suppression, manifestations of Cushing’s syndrome, hyperglycemia, and glucosuria in some patients.

OVERDOSAGE

Topically applied corticosteroids can be absorbed in sufficient amounts to produce systemic effects (see PRECAUTIONS).

DOSAGE AND ADMINISTRATION

Apply a few drops of Betamethasone Dipropionate Lotion USP, 0.05% to the affected area and massage lightly until it disappears. Apply twice daily, in the morning and at night.

Betamethasone Dipropionate Lotion USP, 0.05% is not to be used with occlusive dressings.

HOW SUPPLIED

Betamethasone Dipropionate Lotion USP, 0.05% is available as follows:

60 mL bottle (NDC 45802-021-46)

Shake well before using.

STORAGE

Store at 20-25°C (68-77°F) [see USP Controlled Room Temperature]. Protect from light and freezing. Store in carton until contents are used.

Made in Israel

Manufactured by Padagis
Yeruham, Israel

Distributed By
Padagis
Allegan, MI 49010 • www.padagis.com

Rev 02-22

23JA3 RC F5

Principal Display Panel

Rx Only

Betamethasone Dipropionate Lotion USP, 0.05%

(Potency expressed as Betamethasone)

For Dermatologic Use Only

Not for Ophthalmic Use

NET CONTENTS

60 mL (56.2 g)